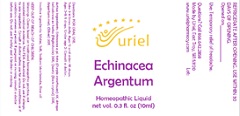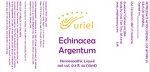 DRUG LABEL: Echinacea Argentum
NDC: 48951-4166 | Form: LIQUID
Manufacturer: Uriel Pharmacy Inc.
Category: homeopathic | Type: HUMAN OTC DRUG LABEL
Date: 20210506

ACTIVE INGREDIENTS: ECHINACEA, UNSPECIFIED 3 [hp_X]/1 mL; SILVER 30 [hp_X]/1 mL; ATROPA BELLADONNA 20 [hp_X]/1 mL; SILICON DIOXIDE 20 [hp_X]/1 mL
INACTIVE INGREDIENTS: WATER; SODIUM CHLORIDE; ROSE OIL; SODIUM BICARBONATE

Echinacea Argentum

INDICATIONS AND USAGE

Directions: FOR ORAL USE.

DOSAGE AND ADMINISTRATION

Take 3-4 times daily. Ages 12 and older: 10 drops. Ages 2-11: 5 drops. Under age 2: Consult a doctor.

ACTIVE INGREDIENT

Active Ingredients: Echinacea e pl. tota (Purple coneflower) 3X, Atropa belladonna ex herba (Nightshade) 20X, Quartz (Rock crystal) 20X, Argentum met. (Silver) 30X

Inactive Ingredients: Water, Salt, Sodium bicarbonate, Rose oil

PURPOSE

Use: Temporary relief of headache.

KEEP OUT OF REACH OF CHILDREN.

WARNINGS

Warnings: Claims based on traditional homeopathic practice, not accepted medical evidence. Not FDA evaluated. Do not use if allergic to any ingredient. Consult a doctor before use for serious conditions or if conditions worsen or persist. If pregnant or nursing, consult a doctor before use. Do not use if safety seal is broken or missing.

REFRIGERATE AFTER OPENING. USE WITHIN 30 DAYS OF OPENING.
Opened on:_________________

Questions? Call 866.642.2858
Made by Uriel, East Troy, WI 53120
www.urielpharmacy.com Lot#